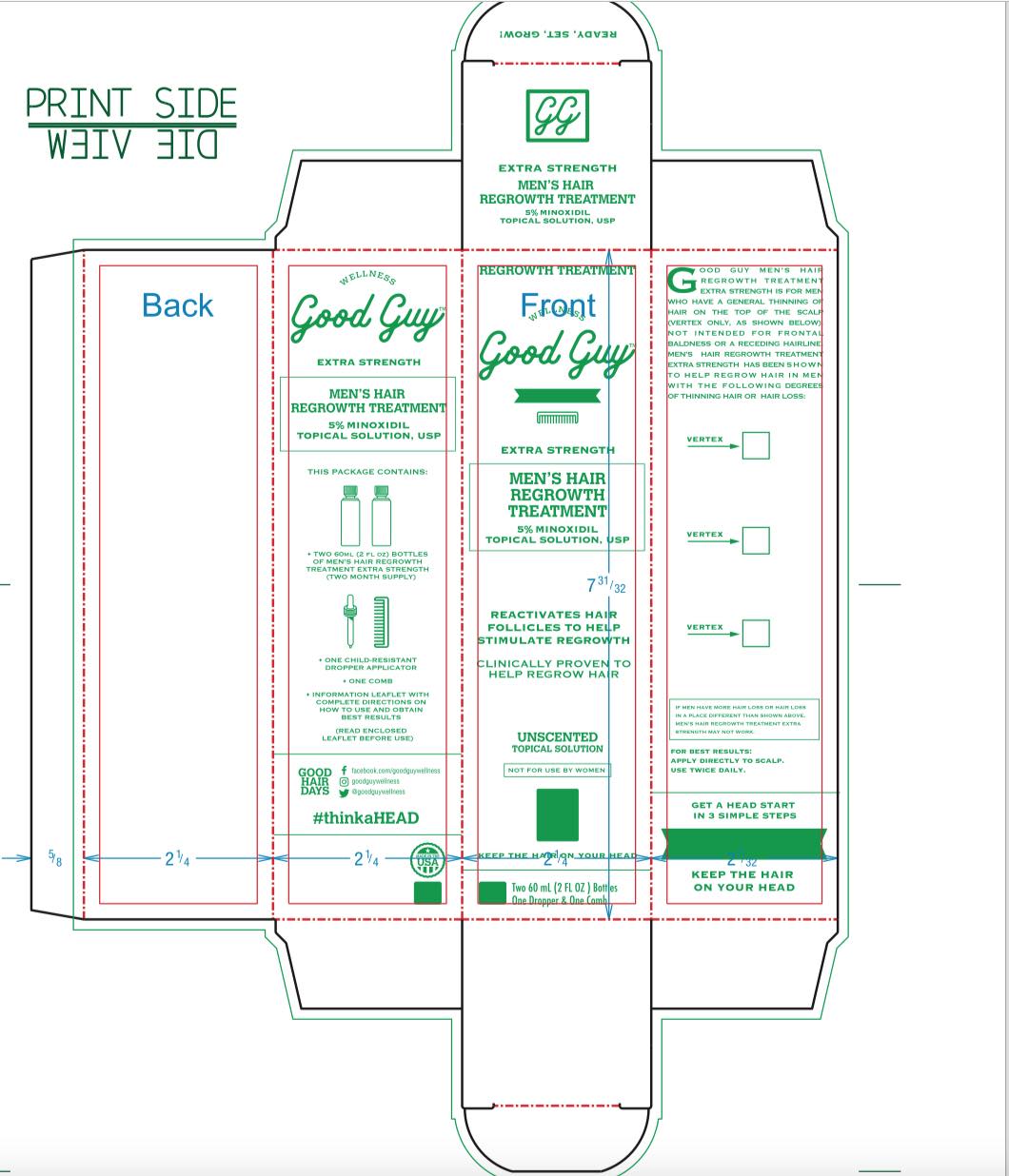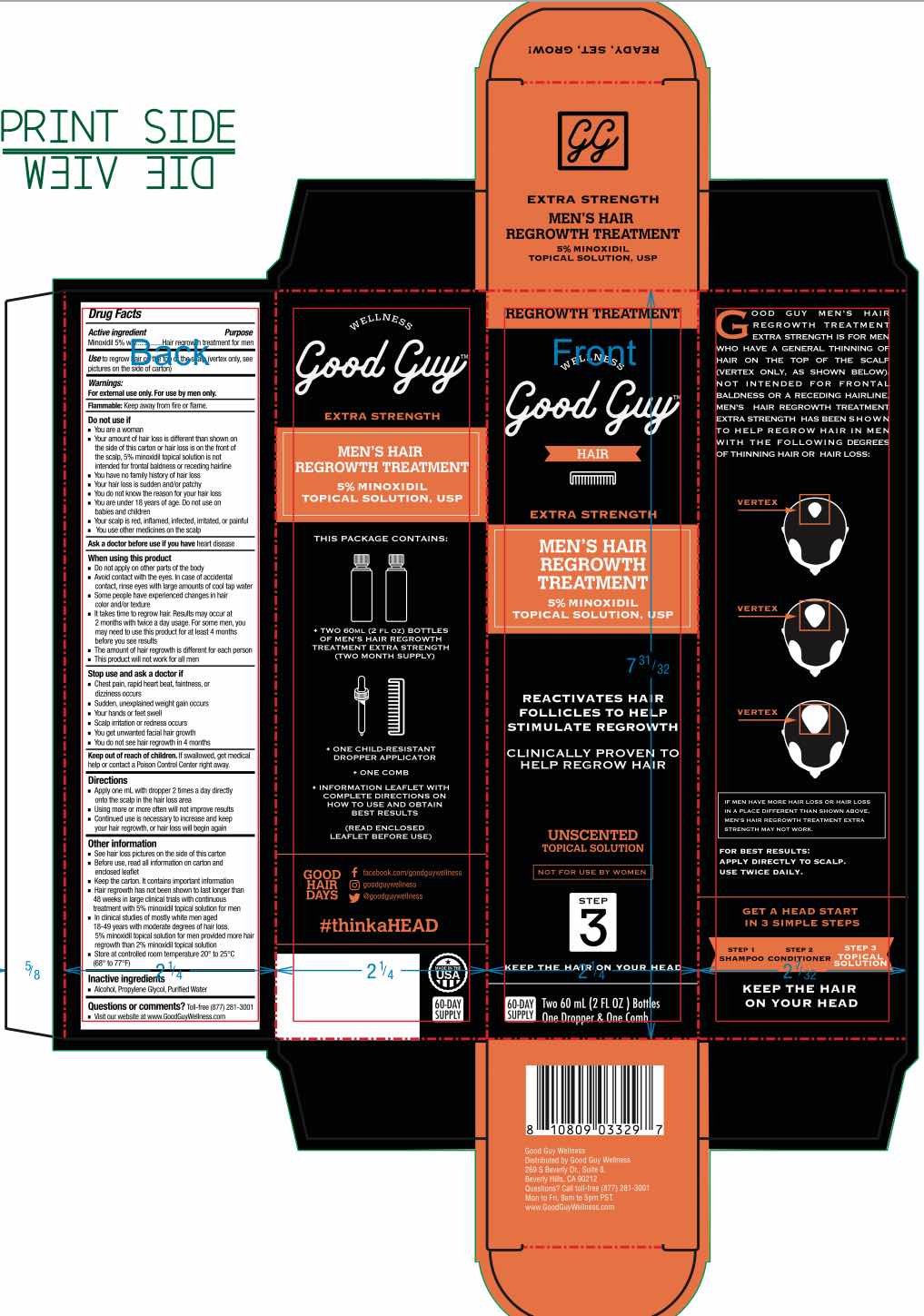 DRUG LABEL: GOOD GUY Mens Hair Regrowth Treatment
NDC: 72764-002 | Form: SOLUTION
Manufacturer: Brandable, Inc.
Category: otc | Type: HUMAN OTC DRUG LABEL
Date: 20230118

ACTIVE INGREDIENTS: MINOXIDIL 5 g/100 mL
INACTIVE INGREDIENTS: WATER; PROPYLENE GLYCOL; ISOPROPYL ALCOHOL

GOOD GUY 5% MINOXIDIL SOLUTION
Men's Hair Regrowth Treatment

ACTIVE INGREDIENT

Minoxidil 5% w/w

PURPOSE

Hair regrowth treatment for men

Use

Use to regrow hair on the top of the scalp (vertex only, see pictures on side of carton)

WARNINGS

For external use only. For use by men only.

Flammable: Keep away from fire or flame.

Do not use if:

- You are a woman
- Your amount of hair loss is different than shown on the side of this carton or hair loss is on the front of the scalp, 5% minoxidil topical solution is not intended for frontal baldness or receding hairline
- You have no family history of hair loss
- Your hair loss is sudden and/or patchy
- You do not know the reason for your hair loss
- You are under 18 years of age. Do not use on babies or children
- Your scalp is red, inflamed, infected, irritated, or painful
- You use other medicines on the scalp

ASK DOCTOR

Ask your doctor before use if you have heart disease.

When using this product

- Do not apply on other parts of the body
- Avoid contact with the eyes. In case of accidental contact, rinse eyes with large amounts of cool tap water
- Some people have expereinced changes in hair color and/or texture
- It takes time to regrow hair. Results may occur at 2 months with twice a day usage. For some men, you may need to use this product for at least 4 months before you see results
- The amount of hair regrowth is different for each person
- This product will not work for all men

Stop use and ask a doctor if

- Chest pain, rapid heart beat, faintness, or dissiness occurs
- Sudden, unexplained weight gain occurs
- Your hands of feet swell
- Scalp irritation or redness occurs
- You get unwanted facial hair growth
- You do not see hair regrowth in 4 months

Directions

- Apply one mL with dropper 2 times a day directly onto the scalp in the hair loss area
- Using more or more ofthen will not improve results
- Continued use is necessary to increase and keep your hair regrowth, or hair loss will begin again

Other Information

- See hair loss pictures on the side of this carton
- Before use, read all information on carton and enclosed leaflet
- Keep the carton. It contains important information
- Hair regrowth has not been shown to last longer than 48 weeks in large clinical trialse with continuous treatment with 5% minoxidil topical solution for men
- In clincial studies of mostly white men aged 18-49 years with moderate degrees of hair loss, 5% minoxidil topical solution for men provide more hair regrowth than 2% minoxidil topical solution
- Store at controlled room temperature 20o to 25oC (68o to 77oF)

Inactive ingredients

- Alcohol, Propylene Glycol, Purified Water

Questions or comments? Toll-free (877) 281-3001

- Visit our website at www.GoodGuyWellness.com

Keep out of reach of children. If swallowed, get medical help or contact a Poison Control Center right away.